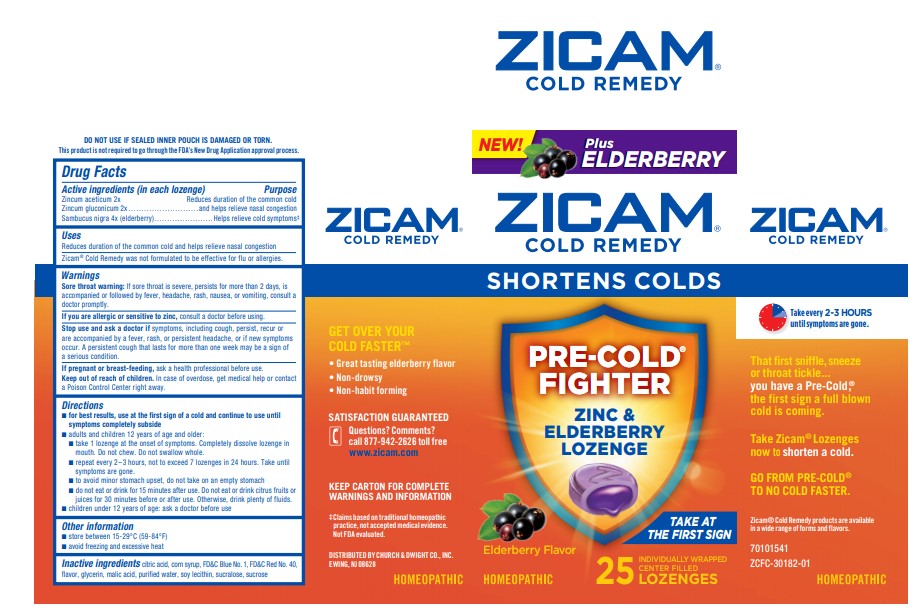 DRUG LABEL: Zicam 
NDC: 10237-462 | Form: LOZENGE
Manufacturer: Church & Dwight Co., Inc.
Category: homeopathic | Type: HUMAN OTC DRUG LABEL
Date: 20240102

ACTIVE INGREDIENTS: ZINC ACETATE ANHYDROUS 2 [hp_X]/1 1; ZINC GLUCONATE 2 [hp_X]/1 1; SAMBUCUS NIGRA FLOWERING TOP 4 [hp_X]/1 1
INACTIVE INGREDIENTS: CITRIC ACID ACETATE; CORN SYRUP; WATER; LECITHIN, SOYBEAN; FD&C BLUE NO. 1 ALUMINUM LAKE; SUCRALOSE; FD&C RED NO. 40; METHYL SALICYLATE; GLYCERIN; MALIC ACID; SUCROSE

Zicam® Cold Remedy Zinc and Elderberry Lozenge

Active ingredients (in each lozenge)

Zincum aceticum 2x

Zincum gluconicum 2x

Sambucus nigra (elderberry) 4x

Purpose

Active ingredients (in each tablet) | Purpose
Zincum aceticum 2x Zincum gluconicum 2x | Reduces duration of the common cold and helps relieve nasal congestion
Sambucus nigra (elderberry) 4x | Helps relieve cold symptoms [Claims based on traditional homeopathic practice, not accepted medical evidence. Not FDA evaluated.]

Uses

Reduces duration of the common cold and helps relieve nasal congestion

------------------------------------------------------------------------------------------------------

Zicam® Cold Remedy was not formulated to be effective for flu and allergies.

Warnings

Sore throat warning: If sore throat is severe, persists for more than 2 days, is accompanied or followed by fever, headache, rash, nausea, or vomiting, consult a doctor promptly.

ASK DOCTOR

If you are allergic or sensitive to zinc, consult a doctor before using.

Stop use and ask a doctor if symptoms, including cough, persist, recur or are accompanied by a fever, rash, or persistent headache, or if new symptoms occur. A persistent cough that lasts for more than one week may be a sign of a serious condition.

PREGNANCY OR BREAST FEEDING

If pregnant or breast-feeding, ask a health professional before use.

Keep out of reach of children. In case of overdose, get medical help or contact a Poison Control Center right away.

Directions

- for best results, use at the first sign of a cold and continue to use until symptoms completely subside
- adults and children 12 years of age and older:
  - take 1 tablet at the onset of symptoms. Completely dissolve lozenge in mouth. Do not chew. Do now swallow whole.
- repeat every 2 – 3 hours, not to exceed 7 tablets in 24 hours. Take until symptoms are gone.
- to avoid minor stomach upset, do not take on an empty stomach
- do not eat or drink for 15 minutes after use. Do not eat or drink citrus fruits or juices for 30 minutes before or after use. Otherwise, drink plenty of fluids.
- children under 12 years of age: ask a doctor before use

Other information

- store between 15-29°C (59-84°F)
- avoid freezing and excessive heat

Inactive ingredients

citric acid, corn syrup, FD&C Blue No. 1, FD&C Red No. 40, flavor, glycerin, malic acid, purified water, soy lecithin, sucralose, sucrose

Questions? Comments?

call 877-942-2626 toll free
www.zicam.com

PRINCIPAL DISPLAY PANEL - 25 INDIVIDUALLY WRAPPED CENTER FILLED LOZENGES

NEW!

Plus ELDERBERRY

ZICAM®

COLD REMEDY

PRE-COLD®

FIGHTER

ZINC &

ELDERBERRY

LOZENGE

Elderberry Flavor

HOMEOPATHIC

TAKE AT

THE FIRST SIGN

25 INDIVIDUALLY WRAPPED

CENTER FILLED

LOZENGES